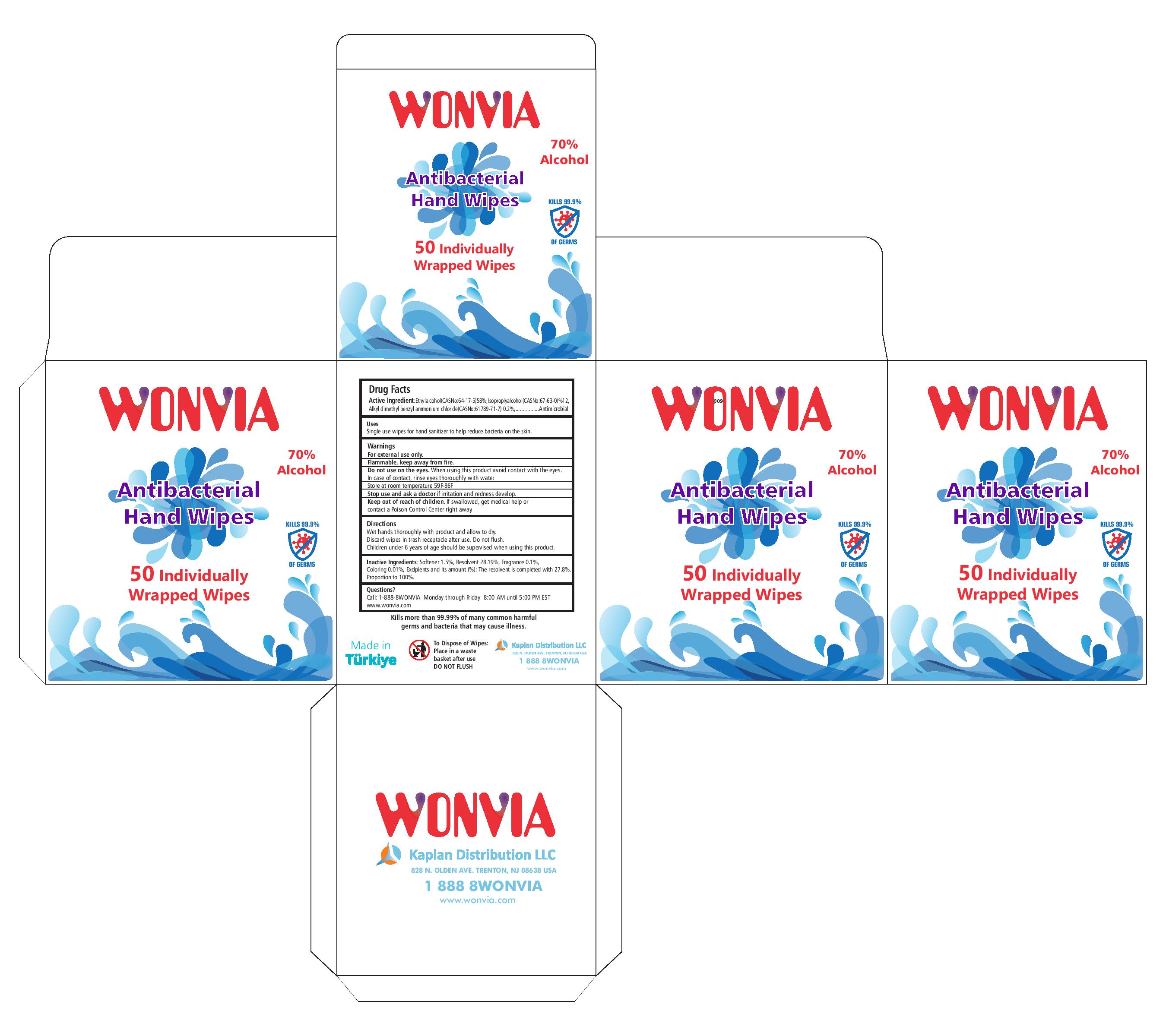 DRUG LABEL: WONVIA INDIVIDUALLY WRAPPED ANTIBACTERIAL HAND WIPES 70% ALCOHOL
NDC: 78876-713 | Form: CLOTH
Manufacturer: KAPLAN DISTRIBUTION LLC
Category: otc | Type: HUMAN OTC DRUG LABEL
Date: 20200908

ACTIVE INGREDIENTS: ALCOHOL 58 g/100 g; BENZALKONIUM CHLORIDE 0.2 g/100 g; ISOPROPYL ALCOHOL 12 g/100 g
INACTIVE INGREDIENTS: WATER

Active Ingredient(s)

Ethyl Alcohol 58%

Isopropyl Alcohol 12%

Alkyl Dimethyl Benzyl Ammonium Chloride 0.2%

Purpose: Antimicrobial

Purpose

Antimicrobial, Hand Wipes

Use

Single-use hand wipes to help reduce bacteria on the skin. For use when soap and water are not available.

Warnings

For external use only. Flammable. Keep away from heat or flame

Do not use

- in children less than 2 months of age
- on open skin wounds

When using this product keep out of eyes, ears, and mouth. In case of contact with eyes, rinse eyes thoroughly with water.
Stop use and ask a doctor if irritation and/or redness develop. These may be signs of a serious condition.
Keep out of reach of children. If swallowed, get medical help or contact a Poison Control Center right away.

Stop use and ask a doctor if irritation and/or redness develop. These may be signs of a serious condition.

Keep out of reach of children. If swallowed, get medical help or contact a Poison Control Center right away.

Directions

- Wet hands thoroughly with product and allow to dry.
- Discard wipes in a trash receptacle after use. Do not flush.
- Children under 6 years of age should be supervised when using this product.

Other information

- Store between 15-30C (59-86F) at room temperature.
- Avoid freezing and excessive heat above 40C (104F)
- Flammable keep away from fire.

Inactive ingredients

Softener 1.5%

Resolvent 28.19%

Fragrance 0.1%

Coloring 0.01%

Excipients and its amount (%): The resolvent is completed 27.8%

Proportion to 100%

Package Label - Principal Display Panel

50 individually wrapped hand wipes= NDC: 78876-713-50